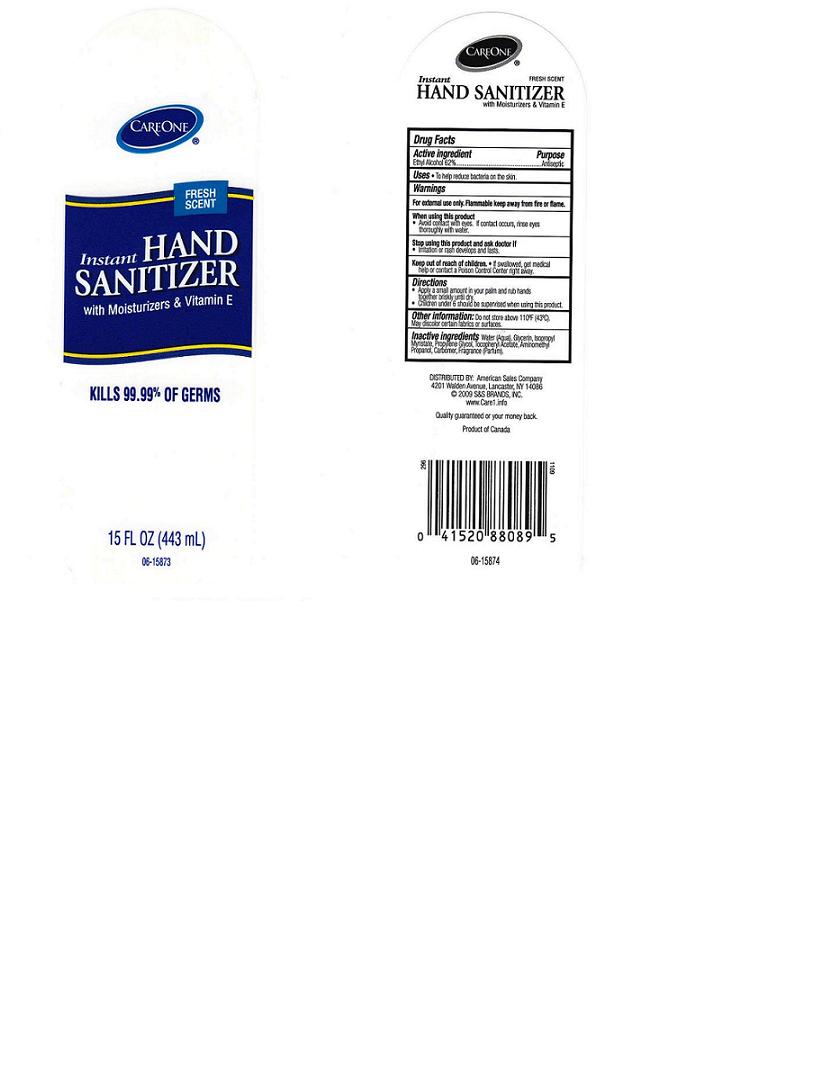 DRUG LABEL: INSTANT HAND SANITIZER
NDC: 63148-225 | Form: GEL
Manufacturer: APOLLO HEALTH AND BEAUTY CARE
Category: otc | Type: HUMAN OTC DRUG LABEL
Date: 20100705

ACTIVE INGREDIENTS: ALCOHOL 62.0000 mL/100 mL

BACK LABEL - DRUG FACTS BOX

ACTIVE INGREDIENT

ETHYL ALCOHOL 62% (ANTISEPTIC)

USES AND DIRECTIONS

- USES: TO HELP REDUCE BACTERIA ON THE SKIN.

- DIRECTIONS: APPLY A SMALL AMOUNT IN YOUR PALM AND RUB HANDS TOGETHER BRISKLY UNTIL DRY. CHILDREN UNDER 6 SHOULD BE SUPERVISED WHEN USING THIS PRODUCT.

WARNINGS

- FOR EXTERNAL USE ONLY.FLAMMABLE KEEP AWAY FROM FIRE OR FLAME.

WHEN USING THIS PRODUCT

- AVOID CONTACT WITH EYES. IF CONTACT OCCURS, RINSE WITH WATER. AVOID CONTACT WITH BROKEN SKIN.

STOP USE AND ASK A DOCTOR IF

- IRRITATION OR RASH DEVELOPS AND LASTS.

KEEP OUT OF REACH OF CHILDREN

- IF SWALLOWED , GET MEDICAL HELP OR CONTACT A POISON CONTROL CENTER RIGHT AWAY.

OTHER INFORMATION

DO NOT STORE ABOVE 110^0F (43^0C). MAY DISCOLOR CERTAIN FABRICS OR SURFACES.

PACKAGE FRONT AND BACK LABELS

- 15OZ FRONT AND BACK LABELS: care15.jpg